DRUG LABEL: White Petrolatum
NDC: 57896-164 | Form: OINTMENT
Manufacturer: Geri-Care Pharmaceuticals, Corp
Category: otc | Type: HUMAN OTC DRUG LABEL
Date: 20241217

ACTIVE INGREDIENTS: PETROLATUM 100 g/100 g

Geri-Care White Petrolatum Ointment

Active Ingredient

White Petrolatum 100%

Purpose

Skin Protectant

Uses

Temporarily protects and relieves

- minor cuts
- scrapes
- burns
- chapped or cracked skin and lips

Helps protect lips from drying effects of wind and cold weather.

Stop use and ask a doctor

Condition worsens

Symptoms last more than 7 days or clear up and occur again with a few days

Keep out of reach of children

If swallowed, get medical help or contact a Poison Control Center right away.

When using this product

Avoid contact with eyes

Inactive Ingredients:

None

Do Not Use

- On deep or puncture wounds
- Animal Bites
- Serious Burns

Directions

Apply as needed

Distributed By

Geri-Care Pharmaceuticals Corp.

1295 Towbin Avenue

Lakewood, NJ. 08701

1-800-540-3765

Warnings

For external use only

Questions

Call: 1-800-540-3765

STORAGE AND HANDLING

Store at room temperature 68º-77ºF (20º-25ºC)

Tamper evident, do not use if packet is torn, cut or opened

Avoid excessive heat and humidity